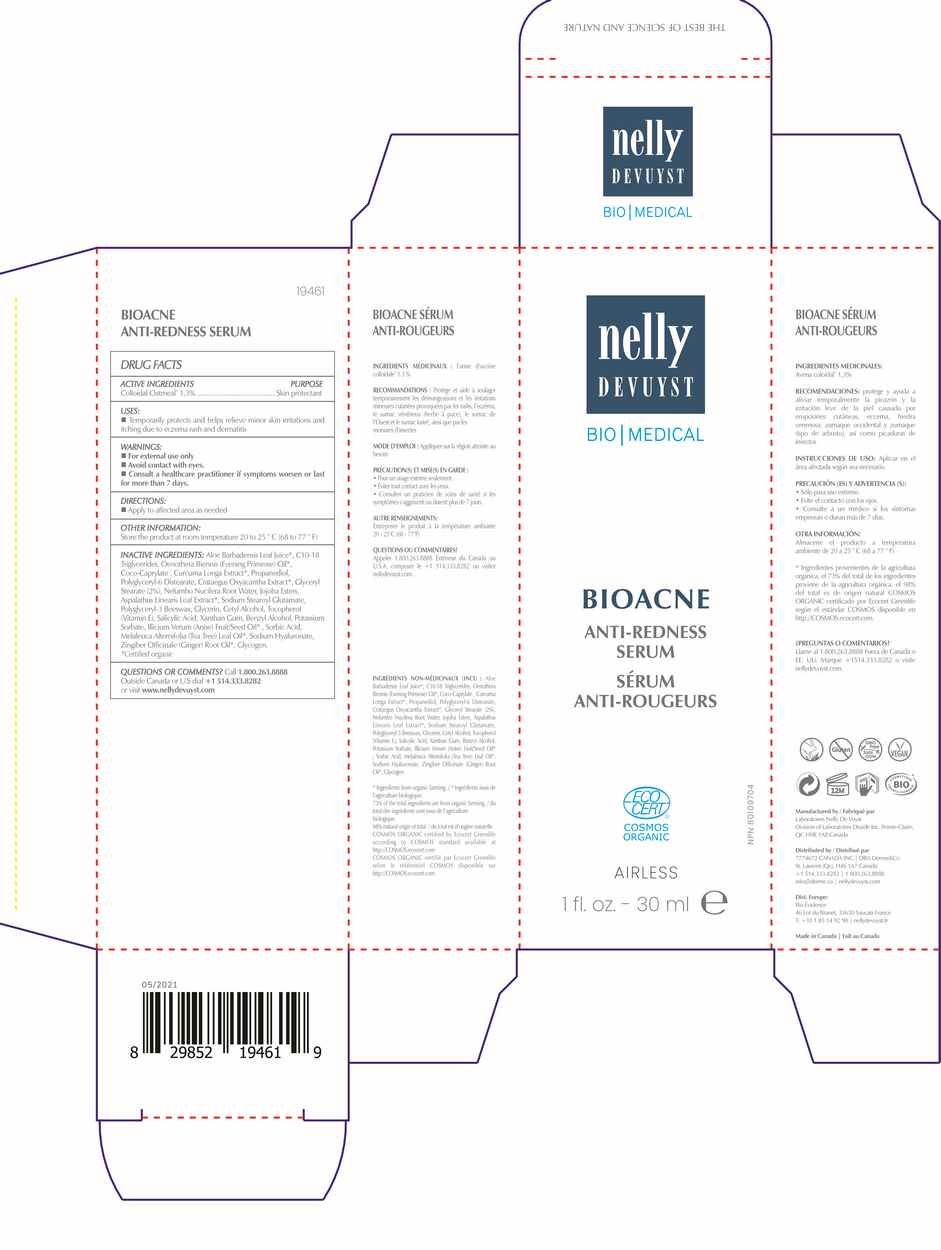 DRUG LABEL: NELLY DEVUYST BIO MEDICAL BIOACNE ANTI-REDNESS SERUM 30 mL
NDC: 71447-030 | Form: CREAM
Manufacturer: LABORATOIRES DRUIDE INC
Category: otc | Type: HUMAN OTC DRUG LABEL
Date: 20211014

ACTIVE INGREDIENTS: OATMEAL 1.3 g/100 g
INACTIVE INGREDIENTS: COCO-CAPRYLATE; TURMERIC; PROPANEDIOL; POLYGLYCERYL-6 DISTEARATE; HAWTHORN LEAF WITH FLOWER; GLYCERYL MONOSTEARATE; NELUMBO NUCIFERA ROOT OIL; JOJOBA OIL, RANDOMIZED; ASPALATHUS LINEARIS LEAF; SODIUM STEAROYL GLUTAMATE; YELLOW WAX; GLYCERIN; CETYL ALCOHOL; TOCOPHEROL; SALICYLIC ACID; XANTHAN GUM; BENZYL ALCOHOL; POTASSIUM SORBATE; STAR ANISE FRUIT; SORBIC ACID; TEA TREE OIL; HYALURONATE SODIUM; GINGER OIL; GLYCOGEN; ASCORBYL GLUCOSIDE

NELLY DEVUYST BIO MEDICAL BIOACNE ANTI-REDNESS SERUM 30 mL

Active Ingredients

Colloidal Oatmeal 1.3%

Purpose

Skin Protectant

Uses

▪ Temporarily protects and helps relieve minor skin irritations and itching due to eczema rash and dermatitis.

Warnings

For external use only

Do not use

Consult a healthcare practitioner if symptoms worsen or last for more than 7 days.

When using this product

keep out of eyes. Rinse with water to remove.

Stop use and ask a doctor if

rash occurs.

Keep out of reach of children

If swallowed, get medical help or contact Poison Control Center right away.

Directions

▪ Apply to affected area as needed.

Other Information

Protect the product in this container from excessive heat and direct sun. Store the product at room temperature 20 to 25°C (68 to 77°F).

Inactive Ingredients

Aloe Barbadensis Leaf Juice*, C10-18 Triglycerides, Oenothera Biennis (Evening Primrose) Oil*, Coco-Caprylate, Curcuma Longa Extract*, Propanediol, Polyglycery1-6 Distearate, Crataegus Oxyacantha Extract*, Crataegus oxyacantha (hawthorn), Glyceryl Stearate (2%), Nelumbo Nucifera Root Water, Jojoba Esters, Aspalathus Linearis Leaf Extract*, Sodium Stearoyl Glutamate, Polyglyceryl-3 Beeswax, Glycerin, Cetyl Alcohol, Tocopherol (Vitamin E), Salicylic Acid, Xanthan Gum, Benzyl Alcohol, Potassium Sorbate, Illicium Verum (Anise) Fruit/Seed Oil* , Sorbic Acid, Melaleuca Alternifolia (Tea Tree) Leaf Oil*, Sodium Hyaluronate, Zingiber Officinale (Ginger) Root Oil*, Glycogen.

*Certified organic.

Questions or Comments?

1-800-263-8888
Outside Canada or the United States dial 514-333-8282 or visit www.nellydevuyst.com